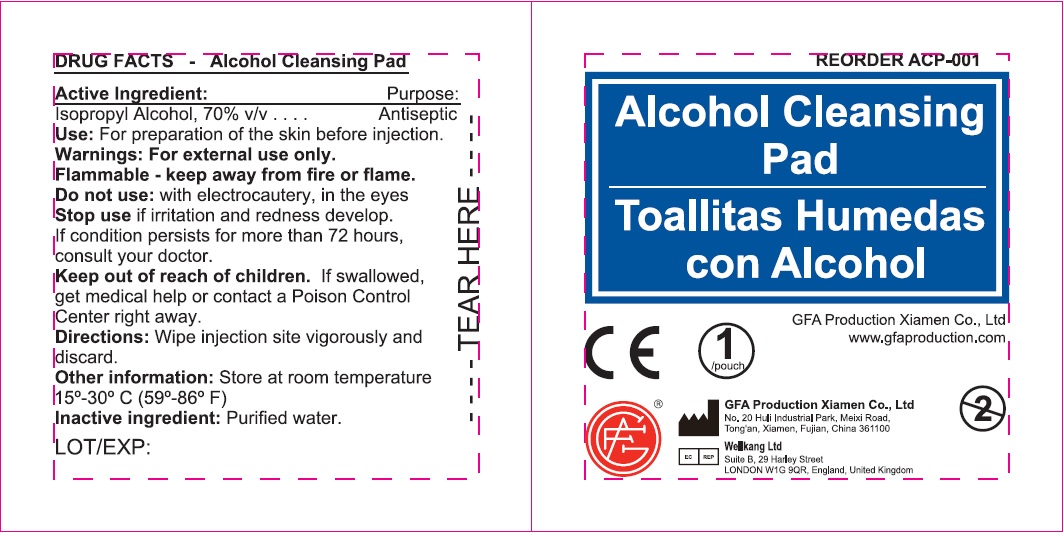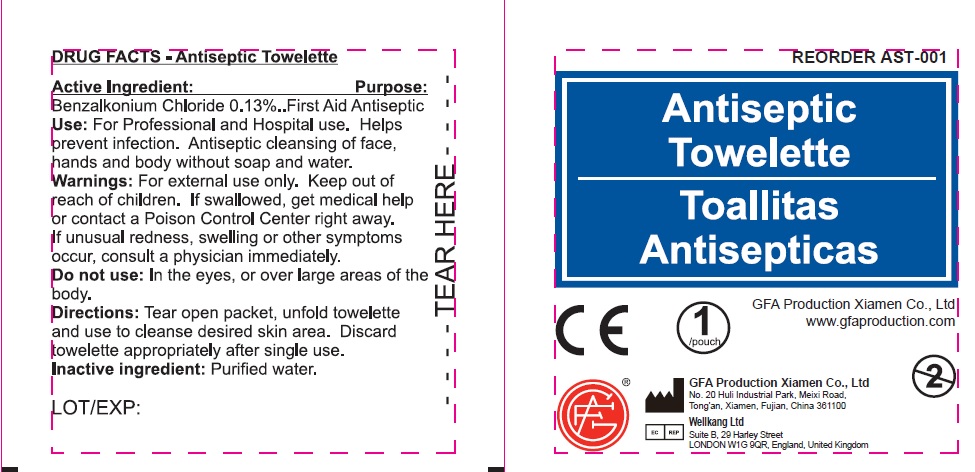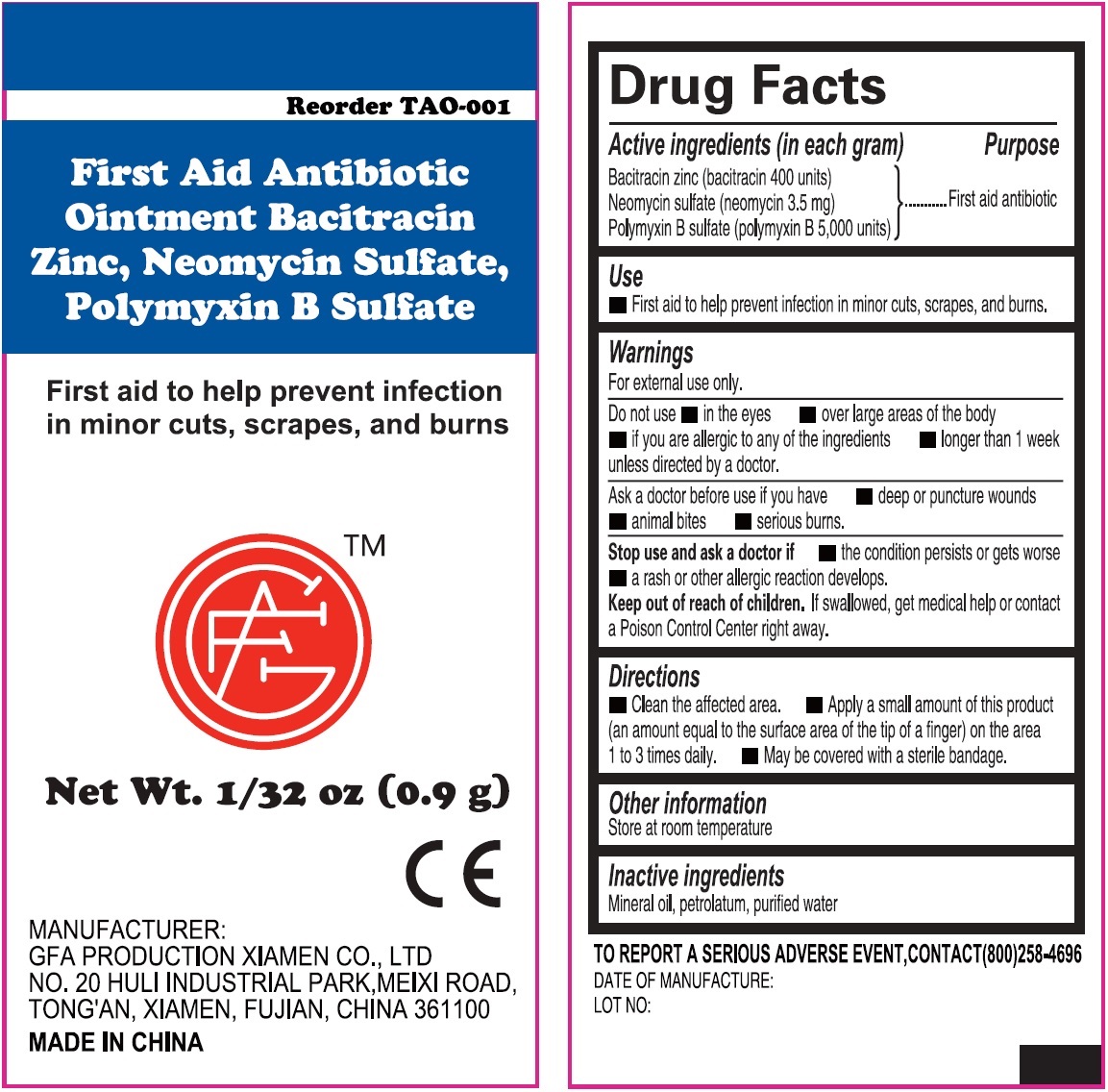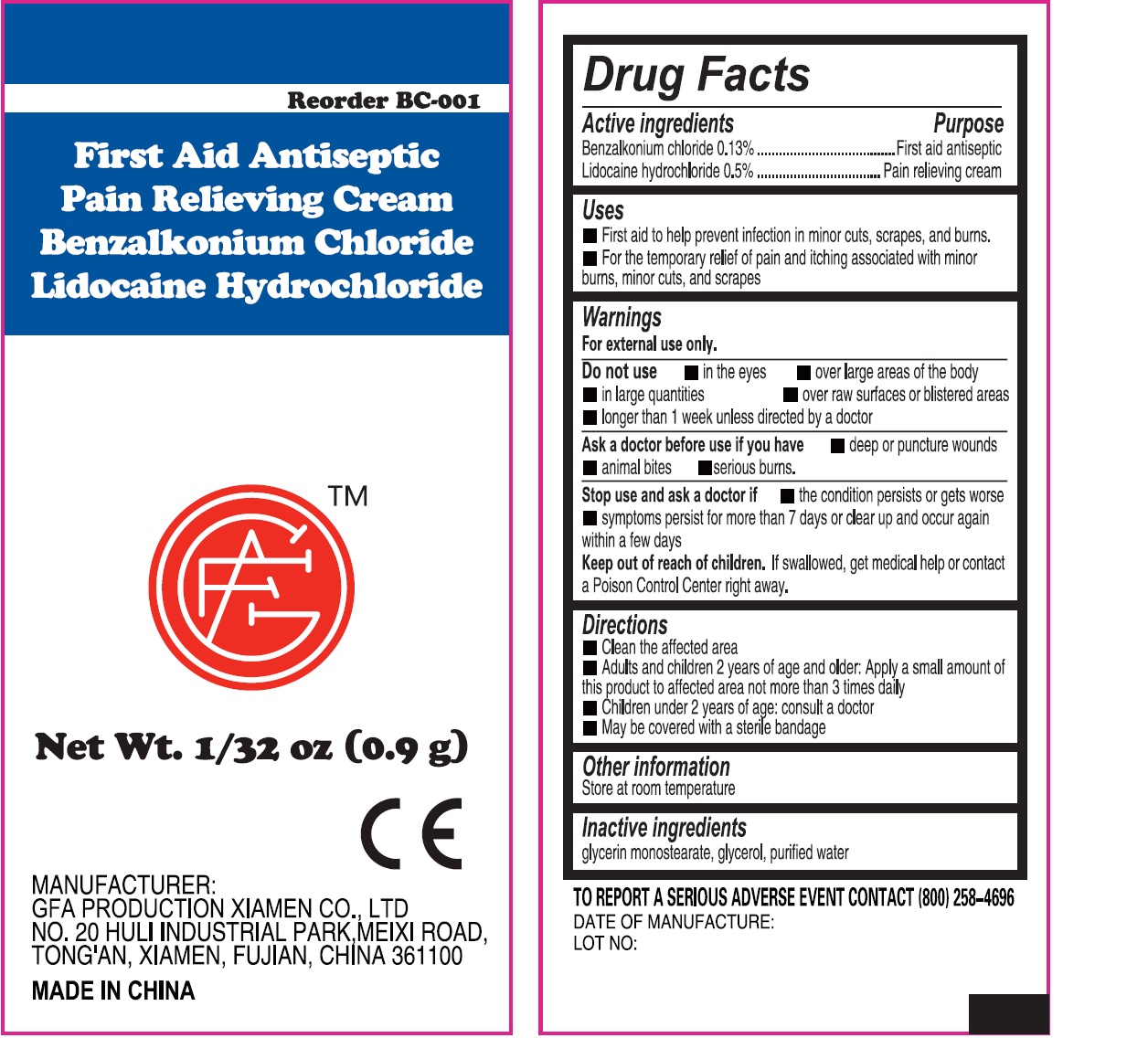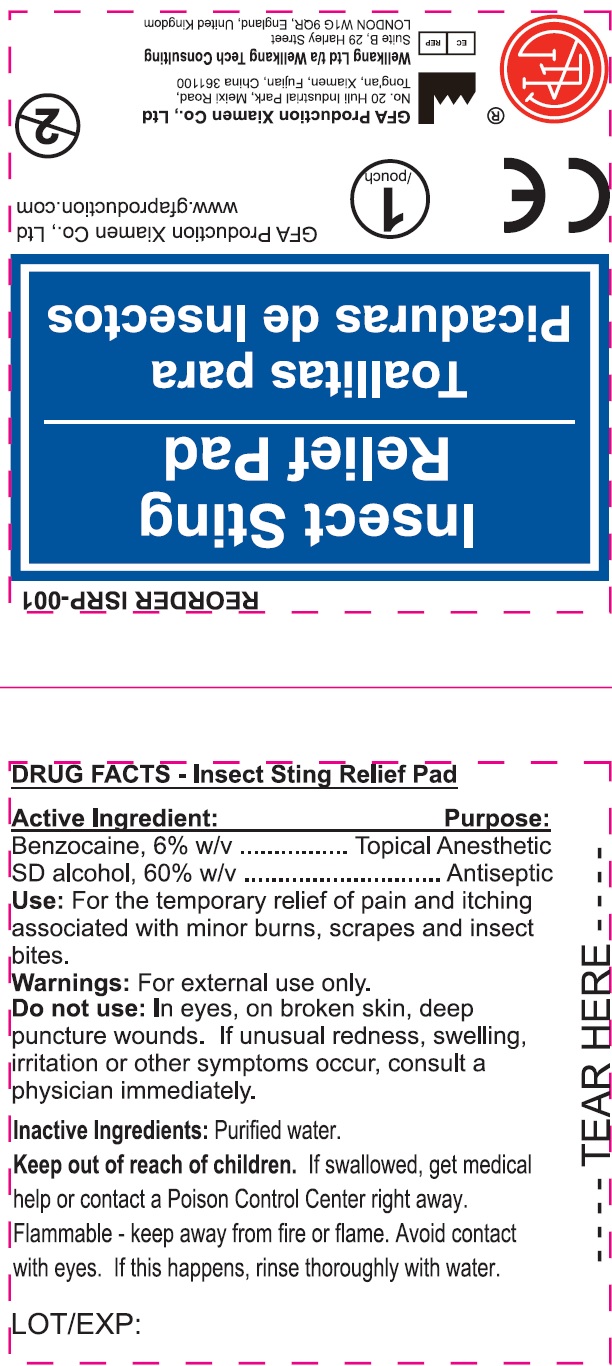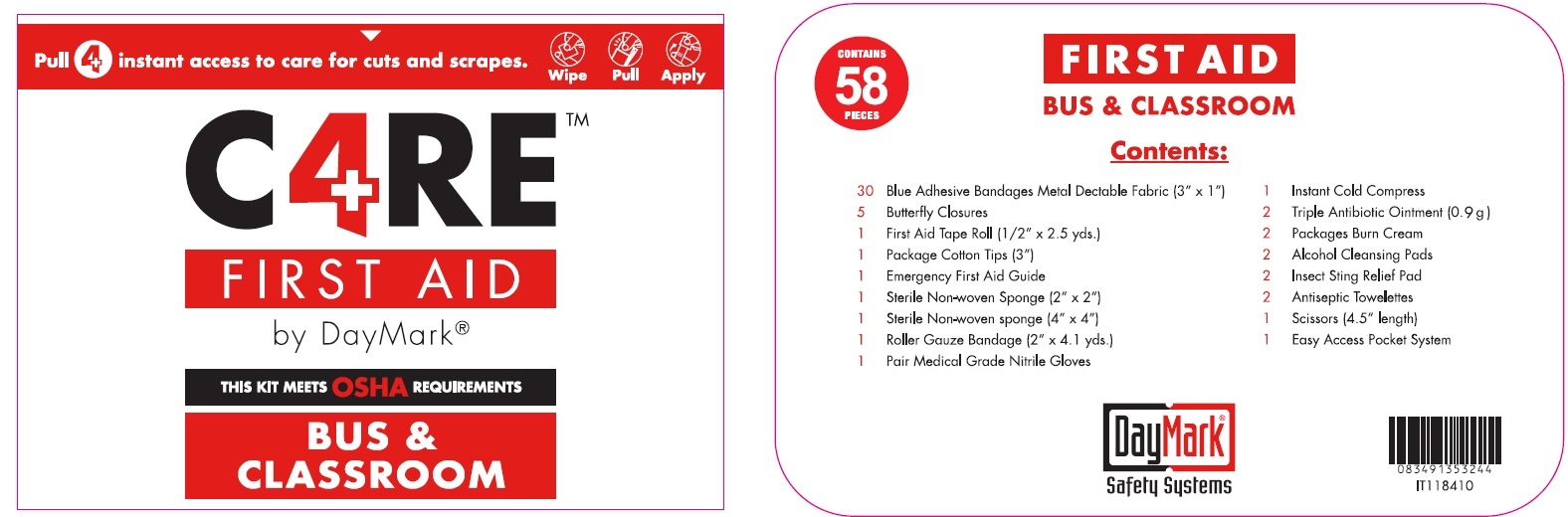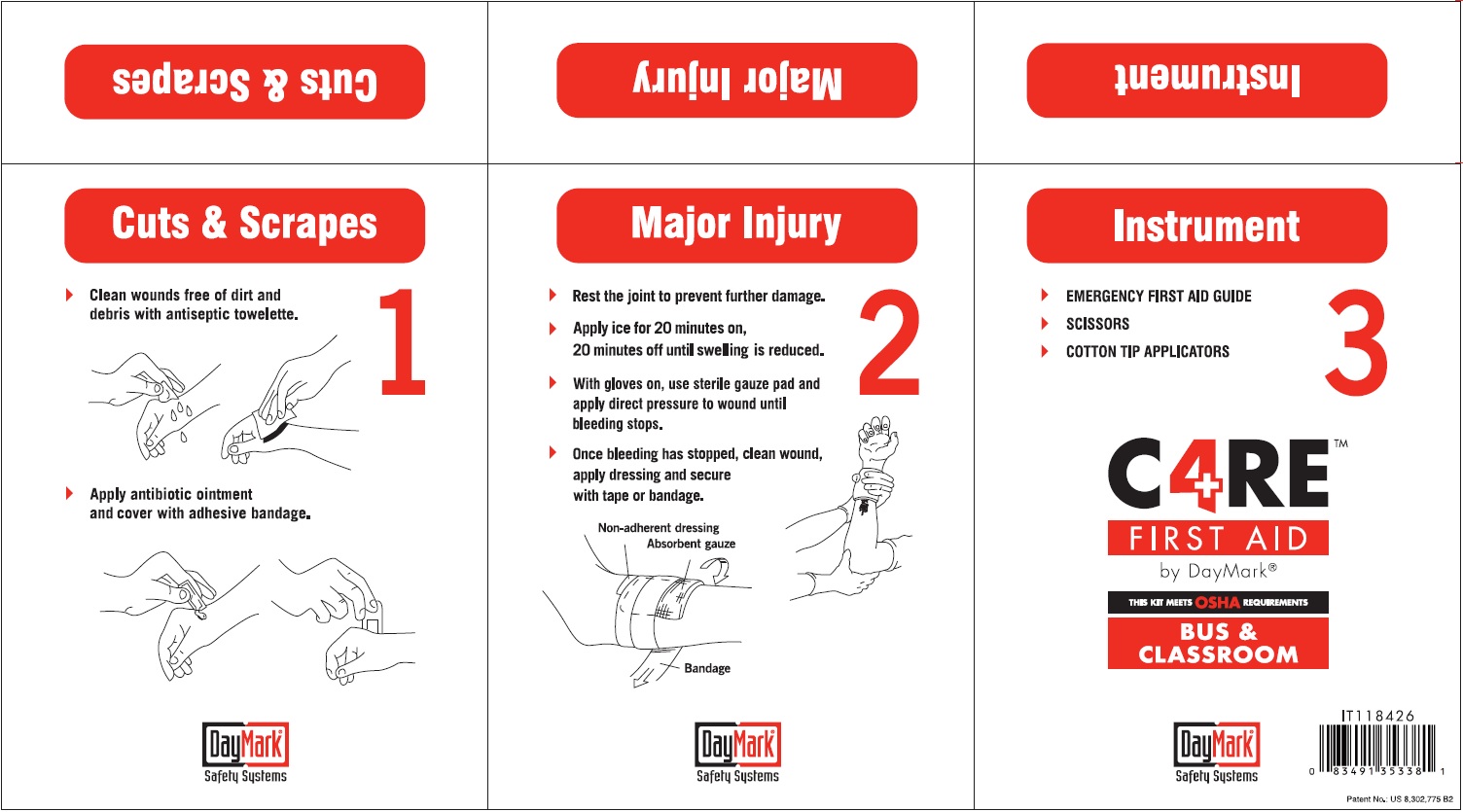 DRUG LABEL: FAK Care4 Bus and School Yellow ORM D
NDC: 50814-042 | Form: KIT | Route: TOPICAL
Manufacturer: GFA Production (Xiamen) Co., Ltd.
Category: otc | Type: HUMAN OTC DRUG LABEL
Date: 20250122

ACTIVE INGREDIENTS: BACITRACIN ZINC 400 [iU]/1 g; NEOMYCIN SULFATE 3.5 mg/1 g; POLYMYXIN B SULFATE 5000 [iU]/1 g; BENZALKONIUM CHLORIDE 1.3 mg/1 g; LIDOCAINE HYDROCHLORIDE 5 mg/1 g; ISOPROPYL ALCOHOL 700 mg/1 g; BENZALKONIUM CHLORIDE 0.13 g/100 g; BENZOCAINE 60 mg/1 mL; ALCOHOL 600 mg/1 mL
INACTIVE INGREDIENTS: MINERAL OIL; PETROLATUM; WATER; GLYCERIN; WATER; WATER; WATER; WATER

FAK Care4 Bus and School Yellow Kit ORM-D

Active ingredients (in each gram)

Bacitracin zinc (bacitracin 400 units)

Neomycin sulfate (neomycin 3.5 mg)

Polymyxin B sulfate (polymyxin B 5,000 units)

Purpose

First aid antibiotic

Use

- First aid to help prevent infection in minor cuts, scrapes, and burns.

Warnings

For external use only.

• Do not use • in the eyes • over large areas of the body • if you are allergic to any of the ingredients

• longer than 1 week unless directed by a doctor.

Ask a doctor before use if you have

• deep or puncture wounds • animal bites • serious burns.

Stop use and ask a doctor if

• the condition persists or gets worse • a rash or other allergic reaction develops.

Keep out of reach of children.

If swallowed, get medical help or contact a Poison Control Center right away.

Directions

• Clean the affected area. • Apply a small amount of this product (an amount equal to the surface area of the tip of a finger) on the area 1 to 3 times daily. • May be covered with a sterile bandage.

Other information

Store at room temperature

Inactive ingredients

Mineral Oil, petrolatum, purified water

Active ingredients

Benzalkonium chloride 0.13%

Lidocaine hydrochloride 0.5

Purpose

First aid antiseptic

Pain relieving cream

Uses

- First aid to help prevent infection in minor cuts, scrapes, and burns.
- For the temporary relief of pain and itching associated with minor burns, minor cuts, and scrapes.

Warnings

For external use only.

Do not use

• in the eyes • over large areas of the body • in large quantities • over raw surfaces or blistered areas • longer than 1 week unless directed by a doctor

Ask a doctor before use if you have

• deep or puncture wounds • animal bites • serious burns.

Stop use and ask a doctor if

• the condition persists or gets worse • symptoms persist for more than 7 days or clear up and occur again within a few days

Keep out of reach of children.

If swallowed, get medical help or contact a Poison Control Center right away.

Directions

- Clean the affected area
- Adults and children 2 years of age and older: Apply a small amount of this product to affected area not more than 3 times daily
- Children under 2 years of age: consult a doctor
- May be covered with a sterile bandage

Other information

Store at room temperature

Inactive ingredients

glycerin monostearate, glycerol, purified water

Active ingredient:

Isopropyl Alcohol, 70% v/v

Purpose

Antiseptic

Use:

For preparation of the skin before injection.

Warnings:

For external use only.

Flammable: keep away from fire or flame.

Do not use:

with electrocautery, in the eyes

Stop use

if irritation and redness develop. if condition persists for more than 72 hours, consult your doctor.

Keep out of reach of children.

If swallowed, get medical help or contact a Poison Control Center right away.

Directions:

Wipe injection site vigorously and discard.

Other information

Store at room temperature 15°-30° C (59°-86° F)

Inactive ingredient:

Purified water.

Active Ingredient:

Benzalkonium Chloride 0.13%

Purpose:

First Aid Antiseptic

Use:

For Professional and Hospital use. Helps prevent infection. Antiseptic cleansing of face, hands and body without soap and water.

Warnings:

For external use only.

Keep out of reach of children.

If swallowed, get medical help or contact a Poison Control Center right away. If unusual redness, swelling or other symptoms occur, consult a physician immediately.

Do not use:

In the eyes, or over large areas of the body.

Directions:

Tear open packet, unfold towelette and use to cleanse desired skin area. Discard towelette appropriately after single use.

Inactive ingredient:

Purified water.

Active Ingredient:

Benzocaine, 6% w/v

SD alcohol, 60% w/v

Purpose

Topical Anesthetic Antiseptic

Use:

For the temporary relief of pain and itching associated with minor burns, scrapes and insect bites.

Warnings:

For external use only.

Do not use:

In eyes, on broken skin, deep puncture wounds. If unusual redness,swelling, irritation or other symptoms occur, consult a physician immediately.

Keep out of reach of children.

If swallowed, get medical help or contact a Poison Control Center right away.

Flammable - keep away from fire or flame. Avoid contact with eyes. If this happens, rinse thoroughly with water.

Inactive Ingredients:

Purified water.